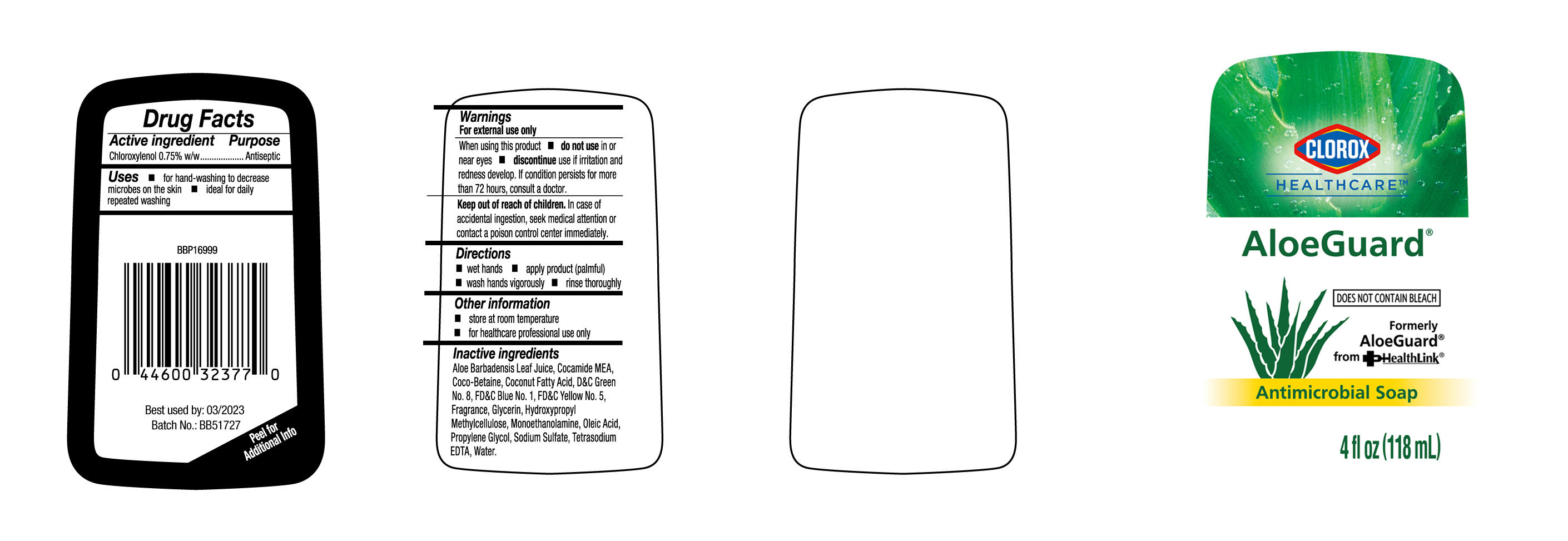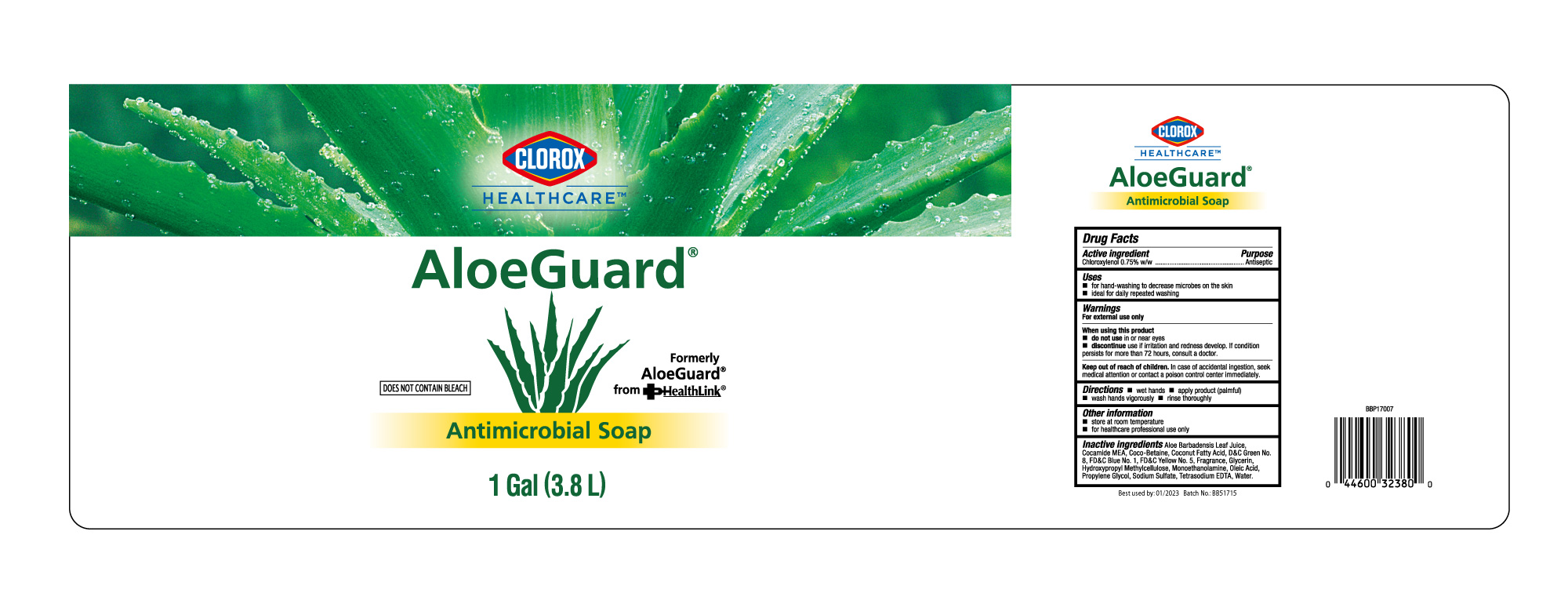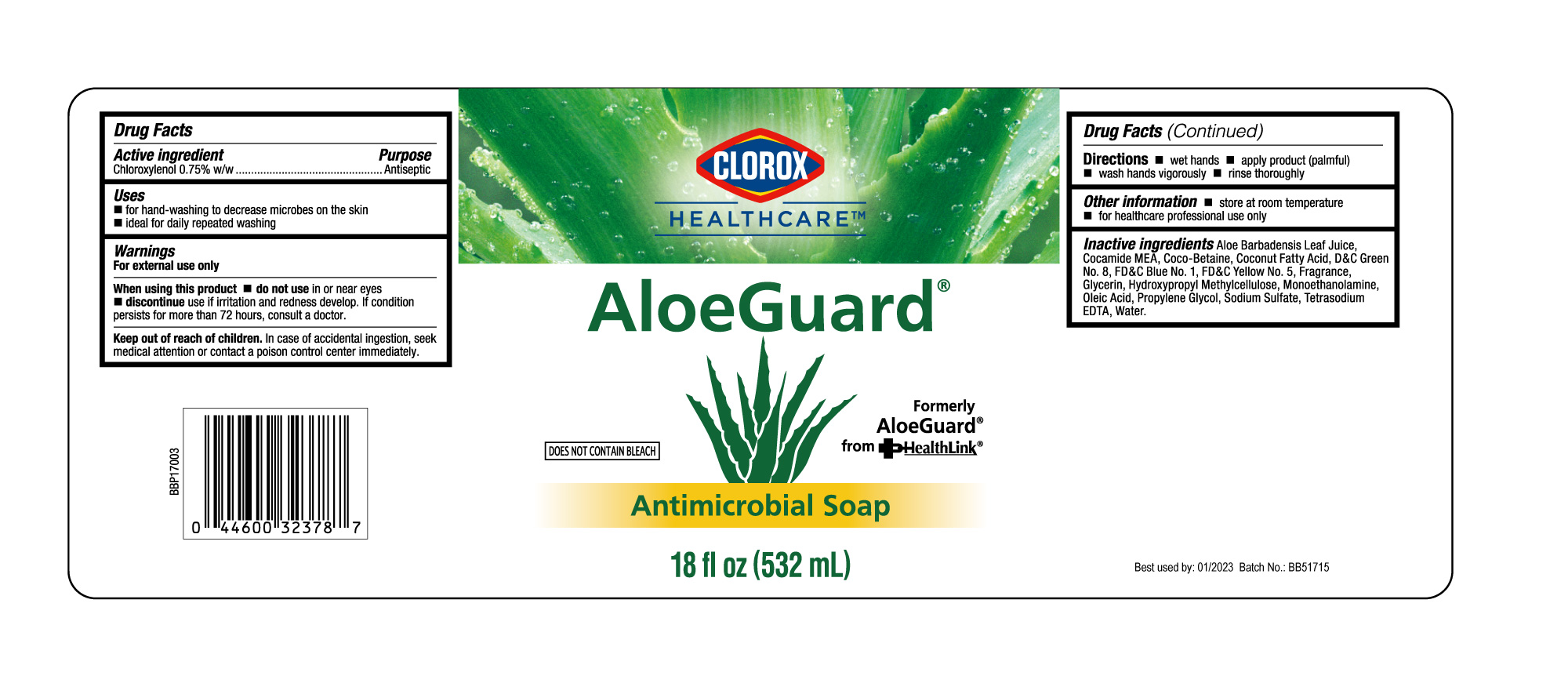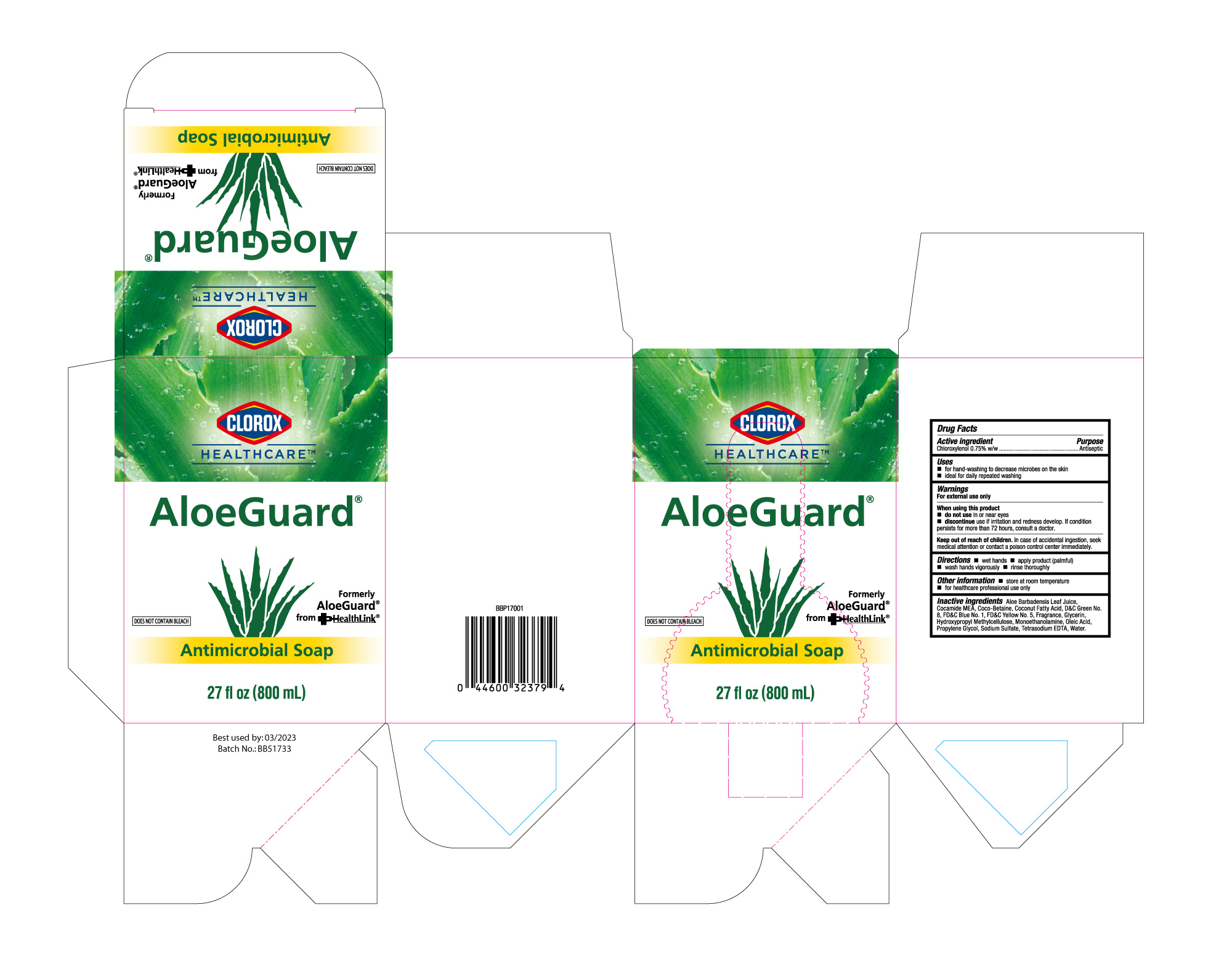 DRUG LABEL: ANTIMICROBIALSOAP
NDC: 47993-325 | Form: GEL
Manufacturer: NINGBO JIANGBEI OCEAN STAR TRADING CO.,LTD
Category: otc | Type: HUMAN OTC DRUG LABEL
Date: 20210617

ACTIVE INGREDIENTS: CHLOROXYLENOL 0.75 g/100 mL
INACTIVE INGREDIENTS: ALOE VERA LEAF; COCO MONOETHANOLAMIDE; COCO-BETAINE; COCO DIETHANOLAMIDE; D&C GREEN NO. 8; FD&C BLUE NO. 1; FD&C YELLOW NO. 5; GLYCERIN; HYPROMELLOSE, UNSPECIFIED; MONOETHANOLAMINE; OLEIC ACID; PROPYLENE GLYCOL; SODIUM SULFATE; EDETATE SODIUM; WATER

47993-325

Active ingredients

Chloroxylenol 0.75% w/w

PURPOSE

Antiseptic

Uses：

- for hand-washing to decrease microbes on the skin.
- ideal for daily repeated washing

Warnings:

For external use only.

When using this product

- do not use in or near eyes.

STOP USE

- discotinue use if irritation and redness develop. If condition persists for more than 72 hours, consult a doctor.

Keep out of reach of children. In case of accidental ingestion, seek medical attention or contact a poison control center immediately.

Directions:

- wet hands
- apply product (palmful)
- wash hands vigorously
- rinse thoroughly

Other information:

- store at room temperature
- for healthcare professional use only

Inactive ingredients:

Aloe Barbadensis Leaf Juice, Cocamide MEA, Coco-Betaine, Coconut Fatty Acid, D&C Green No.8, FD&C Blue No.1, FD&C Yellow No.5, Fragrance, Glycerin, Hydroxypropyl Methylcellulose, Monoethanolamine, Oleic Acid, Propylene Glycol, Sodium Sulfate, Tetrasodium EDTA, Water.